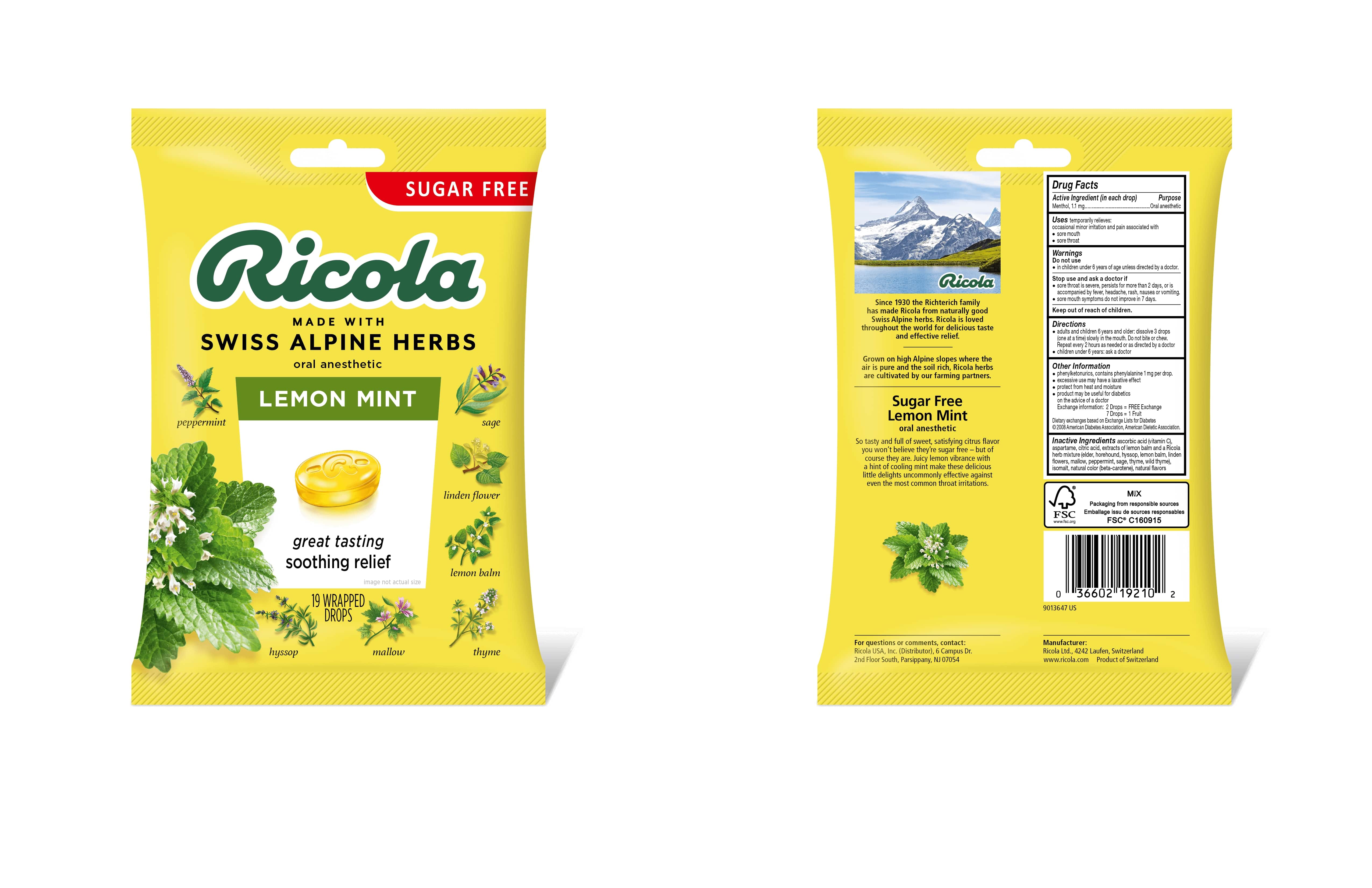 DRUG LABEL: SUGAR FREE LEMON MINT HERB THROAT DROPS
NDC: 54305-102 | Form: LOZENGE
Manufacturer: Ricola Ag
Category: otc | Type: HUMAN OTC DRUG LABEL
Date: 20250422

ACTIVE INGREDIENTS: MENTHOL 1.1 mg/1 1
INACTIVE INGREDIENTS: ASPARTAME; CITRIC ACID MONOHYDRATE; ISOMALT; ASCORBIC ACID

LEMON MINT HERB THROAT DROPS SUGAR FREE

Drug Facts

Purpose

Oral anesthetic

Active Ingredient (in each drop)

Menthol, 1.1 mg

Uses

temporarily relieves occasional minor irritation and pain associated with:

- sore mouth
- sore throat

Warnings

Do not use

- in children under 6 years of age unless directed by a doctor.

Stop use and ask a doctor if

- sore throat is severe, persists for more than 2 days, or is accompanied by fever, headache, rash, nausea or vomiting.
- sore mouth symptoms do not improve in 7 days.

Directions

- adults and children 6 years and older: dissolve 3 drops (one at a time) slowly in the mouth. Repeat every 2 hours as needed or as directed by a doctor
- children under 6 years: ask a doctor

Other Information

- Phenylketonurics: contains phenylalanine 1 mg per drop
- excessive use may have a laxative effect
- store in a dry place
- product may be useful for diabetics on the advice of a doctor

Exchange information: 2 Drops = FREE Exchange

7 Drops = 1 Fruit

Dietary exchanges based on Exchange Lists for Diabetics

© 2008 American Diabetes Association, American Dietetic Association

Inactive Ingredients

ascorbic acid (vitamin C), aspartame, citric acid, extracts of lemon balm and a Ricola herb mixture (elder, horehound, hyssop, lemon balm, linden flowers, mallow, peppermint, sage, thyme, wild thyme), isomalt, natural color (beta-carotene), natural flavors